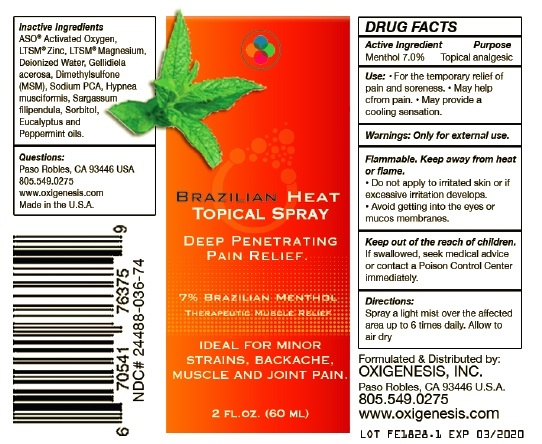 DRUG LABEL: Brazilian Heat
NDC: 72136-001 | Form: LIQUID
Manufacturer: Oxigenesis, Inc
Category: otc | Type: HUMAN OTC DRUG LABEL
Date: 20180327

ACTIVE INGREDIENTS: Menthol 70 mg/1 mL
INACTIVE INGREDIENTS: ALCOHOL; DIMETHYL SULFONE; EUCALYPTUS OIL; GELIDIELLA ACEROSA; HYDROGEN PEROXIDE; CHLORINE DIOXIDE; HYPNEA MUSCIFORMIS; MAGNESIUM; PEPPERMINT OIL; SARGASSUM FILIPENDULA; SODIUM; SORBITOL; WATER; ZINC

Drug Facts

Active Ingredient

Menthol 7.0%

Inactives

Alcohol, Dimethyl Sulfone (MSM),
Eucalyptus Oil, Gelidiella acerosa,
Hydrogen Peroxide and Chlorine
Dioxide, Hypnea musciformis,
Magnesium, Peppermint Oil,
Sargassum filipendula,
Sodium, Sorbitol, Water, Zinc

Purpose

External analgesic

Use

- For the temporary relief of pain and soreness.
- May help distract from pain.
- May provide a cooling sensation.

Warnings

Only for external use.

Flammable. Keep away from heat
or flame.

- Do not apply to irritated skin or if
  excessive irritation develops
- Avoid getting into the eyes or
  mucos membranes.

Directions

Spray a light mist over the affected
area up to 6 times daily. Allow to
air dry.

Keep out of reach children